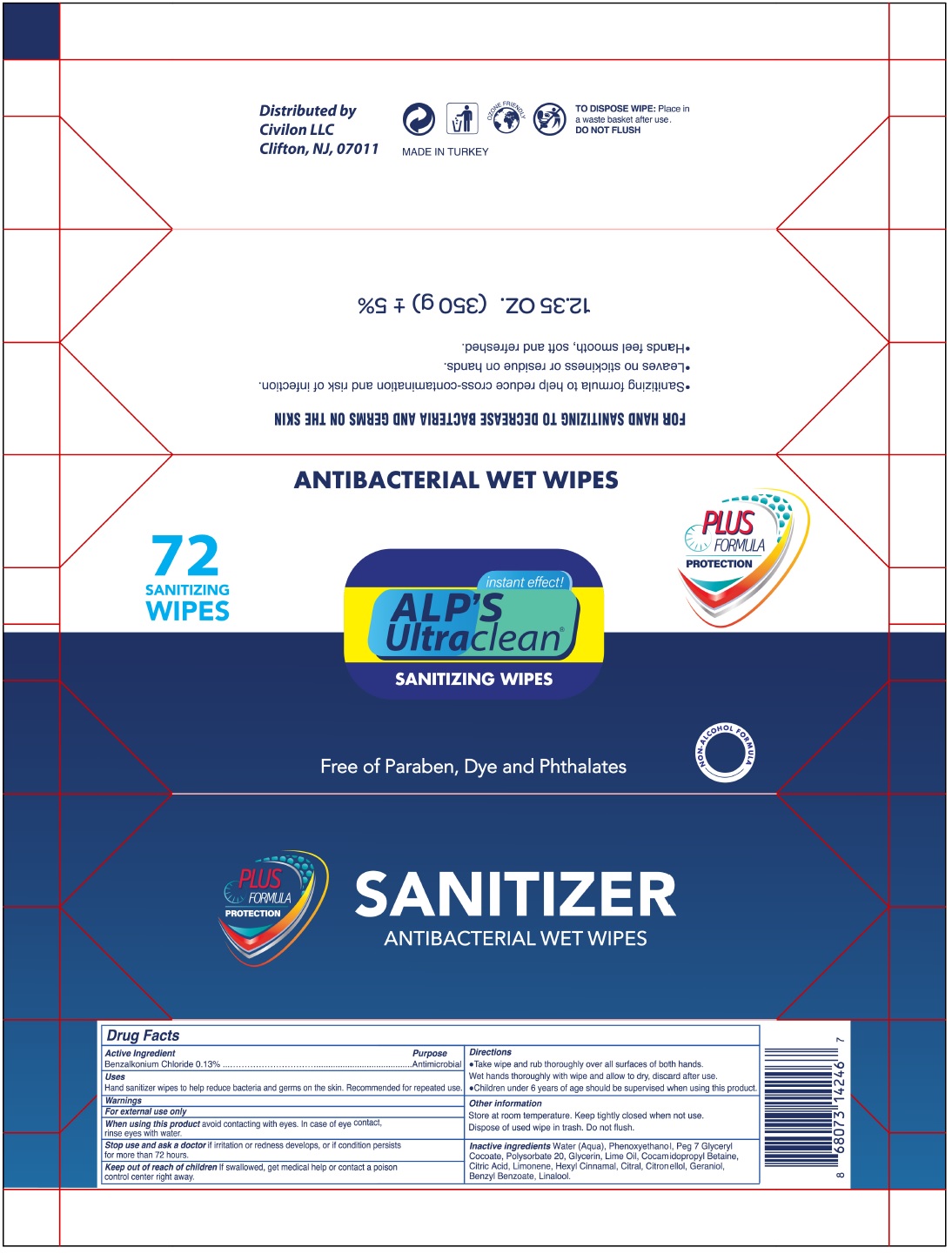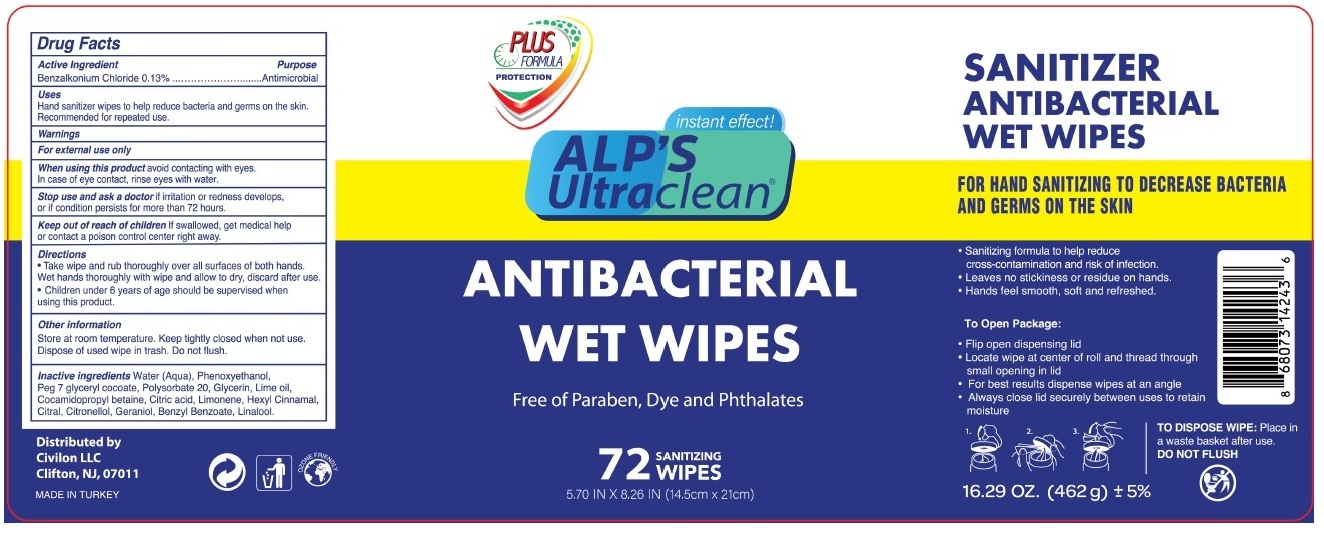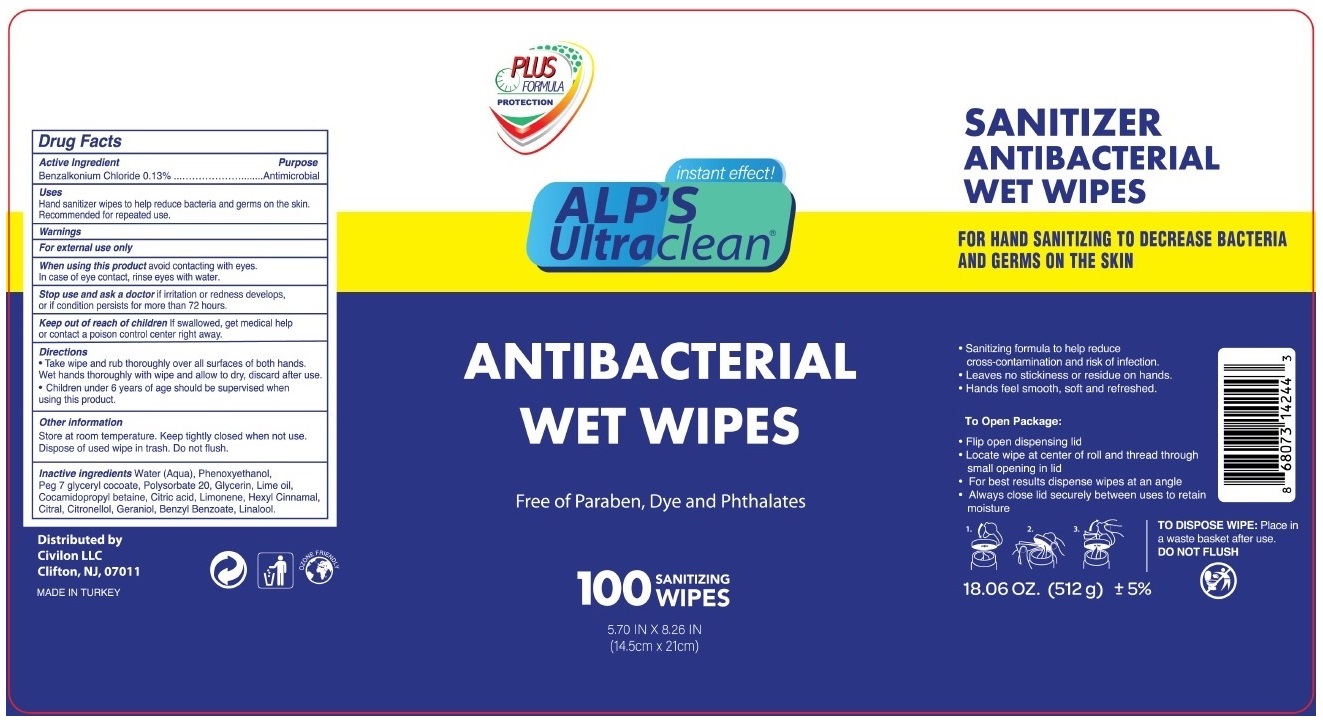 DRUG LABEL: ALPS ULTRACLEAN ANTIBACTERIAL WET WIPES
NDC: 78089-047 | Form: CLOTH
Manufacturer: Endeks Kimya Sanayi Ve Ticaret Anonim Sirketi
Category: otc | Type: HUMAN OTC DRUG LABEL
Date: 20200921

ACTIVE INGREDIENTS: BENZALKONIUM CHLORIDE 0.13 g/100 g
INACTIVE INGREDIENTS: WATER; PHENOXYETHANOL; PEG-7 GLYCERYL COCOATE; POLYSORBATE 20; GLYCERIN; LIME OIL; COCAMIDOPROPYL BETAINE; CITRIC ACID MONOHYDRATE; LIMONENE, (+)-; .ALPHA.-HEXYLCINNAMALDEHYDE; CITRAL; .BETA.-CITRONELLOL, (R)-; GERANIOL; BENZYL BENZOATE; LINALOOL, (+/-)-

ALP'S UltraClean ANTIBACTERIAL WET WIPES

Active Ingredient

Benzalkonium Chloride 0.13%

Purpose

Antimicrobial

Uses

Hand sanitizer wipes to help reduce bacteria and germs on the skin. Recommended for repeated use.

Warnings

For external use only

When using this product avoid contacting with eyes. In case of eye contact, rinse eyes with water.

Stop use and ask a doctor if irritation or redness develops, or if condition persists for more than 72 hours.

Keep out of reach of children If swallowed, get medical help or contact a poison control center right away.

Directions

• Take wipe and rub thoroughly over all surfaces of both hands. Wet hands thoroughly with wipe and allow to dry, discard after use.
• Children under 6 years of age should be supervised when using this product.

Other information

Store at room temperature. Keep tightly closed when not in use. Dispose of used wipe in trash. Do not flush.

INACTIVE INGREDIENT

Inactive ingredients Water (Aqua), Phenoxyethanol, Peg 7 glyceryl cocoate, Polysorbate 20, Glycerin, Lime oil, Cocamidopropyl betaine, Citric acid, Limonene, Hexyl Cinnamal, Citral, Citronellol, Geraniol, Benzyl Benzoate, Linalool.

PLUS

FORMULA

PROTECTION

instant effect!

Free of Paraben, Dye and Phthalates

SANITIZER

ANTIBACTERIAL WE WIPES

FOR HAND SANITIZING TO DECREASE BACTERIA AND GERMS ON THE SKIN

• Sanitizing formula to help reduce cross-contamination and risk of infection.

• Leaves no stickiness or residue on hands.

• Hands feel smooth, soft and refreshed.

To Open Package:

• Flip open dispensing lid

• Locate wipe at center of roll and thread through small opening in lid

• For best results dispense wipes at an angle

• Always close lid securely between uses to retain moisture

TO DISPOSE WIPE: Place in a waste basket after use.

DO NOT FLUSH

Distributed by

Civilon LLC

Clifton, NJ, 07011

MADE IN TURKEY

OZONE FRIENDLY